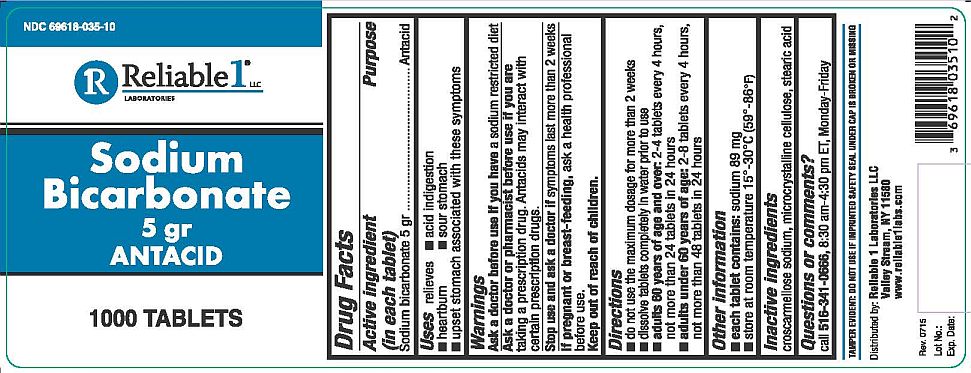 DRUG LABEL: Sodium Bicarbonate 5 gr
NDC: 69618-035 | Form: TABLET, SOLUBLE
Manufacturer: Reliable 1 Laboratories LLC
Category: otc | Type: HUMAN OTC DRUG LABEL
Date: 20210809

ACTIVE INGREDIENTS: SODIUM BICARBONATE 324 mg/1 1
INACTIVE INGREDIENTS: CELLULOSE, MICROCRYSTALLINE; STEARIC ACID; CROSCARMELLOSE SODIUM

Reliable-1 Sodium Bicarbonate 5 gr

Drug Facts

Active ingredient (in each tablet)

Sodium bicarbonate 5 gr

Purpose

Antacid

INDICATIONS AND USAGE

Uses relieves

- acid indigestion
- heartburn
- sour stomach
- upset stomach associated with these symptoms

Warnings

Ask a doctor before use if you have a sodium restricted diet

Ask a doctor or pharmacist before use if you are taking a prescription drug. Antacids may interact with certain prescription drugs.

Stop use and ask a doctor if symptoms last more than 2 weeks

PREGNANCY OR BREAST FEEDING

If pregnant or breast-feeding, ask a health professional before use.

Keep out of reach of children.

Directions

- do not use the maximum dosage for more than 2 weeks
- dissolve tablets completely in water prior to use
- adults 60 years of age and over: 2-8 tablets every 4 hours, not more than 24 tablets in 24 hours
- adults under 60 years of age: 2-8 tablets every 4 hours, not more than 48 tablets in 24 hours

Other information

- each tablet contains: sodium 89 mg
- store at room temperature 15°-30°C (59°-86°F)

Inactive ingredients

croscarmellose sodium, microcrystalline cellulose, stearic acid

Questions or comments?

call 516-341-0666, 8:30 am-4:30 pm ET, Monday-Friday

TAMPER EVIDENT: DO NOT USE IF IMPRINTED SAFETY SEAL UNDER CAP IS BROKEN OR MISSING

Distributed by: Reliable 1 Laboratories LLC

Valley Stream, NY 11580

www.reliable1labs.com

PACKAGE LABEL

NDC 69618-035-10

Sodium Bicarbonate 5 gr

ANTACID

1000 TABLETS